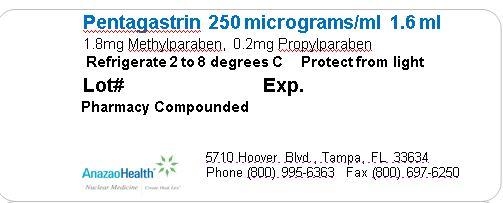 DRUG LABEL: Pentagastrin
NDC: 51808-207 | Form: SOLUTION
Manufacturer: AnazaoHealth Corporation
Category: prescription | Type: HUMAN PRESCRIPTION DRUG LABEL
Date: 20120619

ACTIVE INGREDIENTS: PENTAGASTRIN 250 ug/1.6 mL
INACTIVE INGREDIENTS: METHYLPARABEN 1.8 mg/1.6 mL; PROPYLPARABEN 0.2 mg/1.6 mL

Pentagastrin

DESCRIPTION

Pentagastrin, a diagnostic aid, is supplied as a sterile solution (1.1 ml/5 ml vial) containing:

- 250 micrograms Pentagastrin per ml
- 0.8 mg Methylparaben and 0.2 mg Propylparaben per mL
- 0.9 mg sodium chloride per mL
- pH 8

CLINICAL PHARMACOLOGY

The exact mechanism by which Pentagastrin stimulates gastric acid, pepsin, and intrinsic factor secretion is unknown; however, since Pentagastrin is an analogue of natural gastrin, it is believed that it excites the oxyntic cells of the stomach to secrete to their maximum capacity. Pentagastrin stimulates pancreatic secretion, especially when administered in large intramuscular doses. Pentagastrin also increases gastrointestinal motility by a direct effect on the intestinal smooth muscle. However, it delays gastric emptying time probably by stimulation of terminal antral contractions, which enhance retropulsion.

OTHER ACTIONS/EFFECTS Pentagastrin increases blood flow in the gastric mucosa, inhibits absorption of water and electrolytes from the ileum, and promotes sodium and chloride diuresis. It causes contraction of the smooth muscle of the lower esophageal sphincter when administered intravenously. Pentagastrin produces an increase in the motor activity of the colon and rectum

ONSET OF ACTION 10 minutes

TIME TO PEAK EFFECT 20 to 30 minutes

DURATION OF ACTION 60 to 80 minutes

INDICATIONS AND USAGE

1. Anacidity (diagnosis)—Pentagastrin is indicated as a diagnostic aid for evaluation of gastric acid secretory function. It is effective in testing for anacidity (achlorhydria) in patients with suspected pernicious anemia, atrophic gastritis, or gastric carcinoma. It is also effective in determining the reduction in acid output after operations for peptic ulcer, such as vagotomy or gastric resection.
2. Hypersecretory conditions, gastric (diagnosis)—Pentagastrin is indicated as a diagnostic aid in testing for gastric hypersecretion in patients with suspected duodenal ulcer or postoperative stomal ulcer, and for the diagnosis of Zollinger-Ellison tumor

DOSAGE AND ADMINISTRATION

The intravenous infusion dose has ranged from 0.1 to 12 mcg (0.0001 to 0.012 mg) per kg of body weight per hour administered in a 0.9% sodium chloride injection. It can also be used as a subcutaneous injection for gastric function study with a dose of 6 mcg (0.006 mg) per kg of body weight.

INTERACTIONS

The following may affect pentagastrin’s action:

- Antacids, anticholinergics, histamine H2-receptor antagosnists, or omeprazole
- Acute, obstructing, penetrating or bleeding peptic ulcers

Storage and Handling

Keep refrigerated between 2◦ and 8◦C. Protect from light

PACKAGE LABEL.PRINCIPAL DISPLAY PANEL

Figure 1